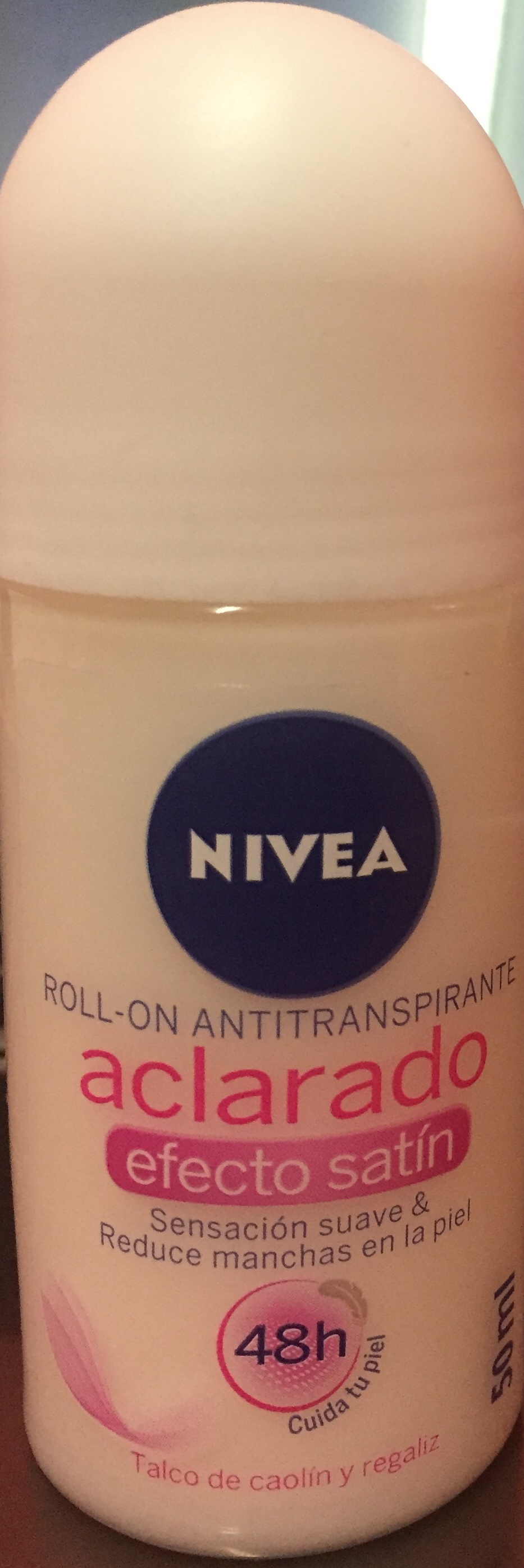 DRUG LABEL: Nieva Satin
NDC: 69772-110 | Form: LIQUID
Manufacturer: Genesis Imports & Exports LLC
Category: otc | Type: HUMAN OTC DRUG LABEL
Date: 20171228

ACTIVE INGREDIENTS: ALUMINUM CHLOROHYDRATE 12.5 g/100 mL
INACTIVE INGREDIENTS: WATER; STEARETH-21; SODIUM ASCORBYL PHOSPHATE; KAOLIN; GLYCYRRHIZA GLABRA; GLYCERIN; EDETATE TRISODIUM; STEARETH-2; PPG-15 STEARYL ETHER

ACTIVE INGREDIENT

Aluminium Chorhydrate

PURPOSE

Antiperspirant

DOSAGE AND ADMINISTRATION

Reduse underarm perspiration

keep Out of reach of children

WARNINGS

Fpr external use only. No apply on irrited or injured skin.

Discountinue use if you experience some irritation. Redness or discomfort

INDICATIONS AND USAGE

Apply under arm only

Shake before use

INACTIVE INGREDIENT

Water, PPG-15 steary ether, steareth 2

steareth 21, glyrrhiza globra, sodium ascorbyl phosphate

kaolin, glycerin, trisodium EDTa